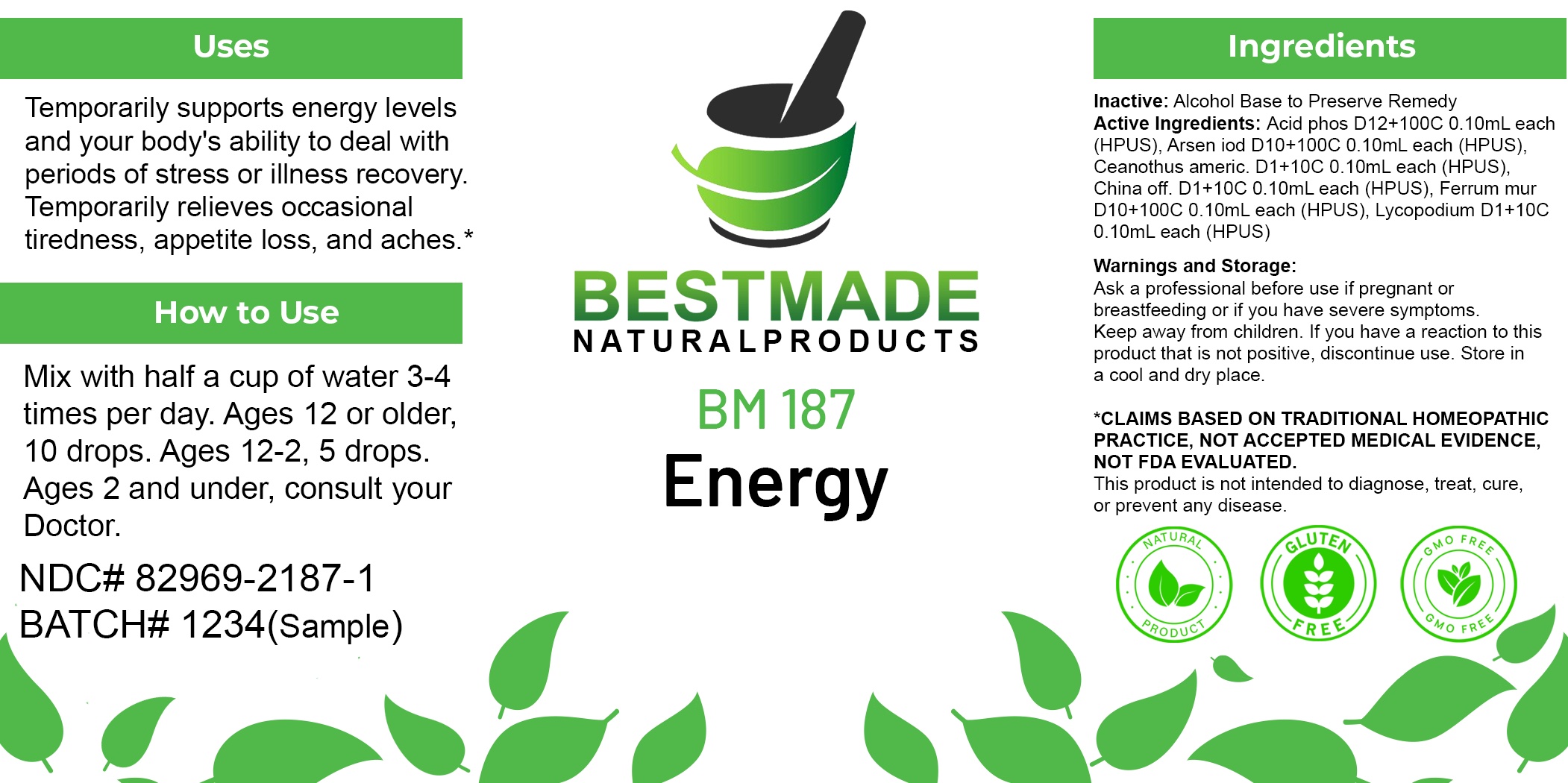 DRUG LABEL: Bestmade Natural Products BM187
NDC: 82969-2187 | Form: LIQUID
Manufacturer: Bestmade Natural Products
Category: homeopathic | Type: HUMAN OTC DRUG LABEL
Date: 20250220

ACTIVE INGREDIENTS: CINCHONA OFFICINALIS BARK 30 [hp_C]/30 [hp_C]; FERRIC CHLORIDE HEXAHYDRATE 30 [hp_C]/30 [hp_C]; LYCOPODIUM CLAVATUM SPORE 30 [hp_C]/30 [hp_C]; CEANOTHUS AMERICANUS LEAF 30 [hp_C]/30 [hp_C]; ARSENIC TRIIODIDE 30 [hp_C]/30 [hp_C]; PHOSPHORIC ACID 30 [hp_C]/30 [hp_C]
INACTIVE INGREDIENTS: ALCOHOL 30 [hp_C]/30 [hp_C]

BM187

DOSAGE AND ADMINISTRATION

How to Use

Mix with half a cup of water 3-4 times per day. Ages 12 or older, 10 drops. Ages 12-2, 5 drops. Ages 2 and under, consult your Doctor.

Inactive:

Alcohol Base to Preserve Product

ACTIVE INGREDIENT

Active Ingredients: Acid phos D12+100C 0.10mL each (HPUS), Arsen iod D10+100C 0.10mL each (HPUS), Ceanothus americ. D1+10C 0.10mL each (HPUS), China off. D1+10C 0.10mL each (HPUS), Ferrum mur D10+100C 0.10mL each (HPUS), Lycopodium D1+10C 0.10mL each (HPUS)

KEEP OUT OF REACH OF CHILDREN

Warnings and Storage:

Ask a professional before use if pregnant or breastfeeding or if you have severe symptoms.

Keep away from children. If you have a reaction to this product that is not positive, discontinue use. Store in a cool and dry place

*CLAIMS BASED ON TRADITIONAL HOMEOPATHIC PRACTICE, NOT ACCEPTED MEDICAL EVIDENCE NOT FDA EVALUATED.
This product is not intended to diagnose, treat, cure, or prevent any disease.

Warnings and Storage:

Ask a professional before use if pregnant or breastfeeding or if you have severe symptoms.

Keep away from children. If you have a reaction to this product that is not positive, discontinue use. Store in a cool and dry place

*CLAIMS BASED ON TRADITIONAL HOMEOPATHIC PRACTICE, NOT ACCEPTED MEDICAL EVIDENCE NOT FDA EVALUATED.
This product is not intended to diagnose, treat, cure, or prevent any disease.

Uses
Temporarily supports energy levels and your body's ability to deal with periods of stress or illness recovery. Temporarily relieves occasional tiredness, appetite loss, and aches.*

Uses
Temporarily supports energy levels and your body's ability to deal with periods of stress or illness recovery. Temporarily relieves occasional tiredness, appetite loss, and aches.*

Entire package label